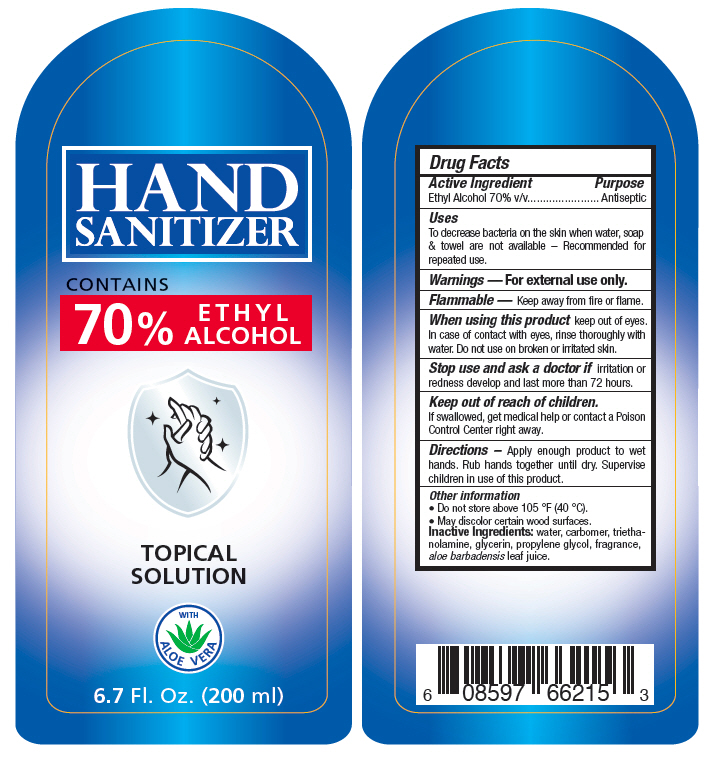 DRUG LABEL: Hand Sanitizer
NDC: 75625-001 | Form: GEL
Manufacturer: Doctor Fashion SAPI de CV
Category: otc | Type: HUMAN OTC DRUG LABEL
Date: 20200722

ACTIVE INGREDIENTS: ALCOHOL 70 mL/100 mL
INACTIVE INGREDIENTS: water; CARBOMER HOMOPOLYMER, UNSPECIFIED TYPE; trolamine; glycerin; propylene glycol; aloe vera leaf

Hand Sanitizer

Drug Facts

Active Ingredient

Ethyl Alcohol 70% v/v

Purpose

Antiseptic

Uses

To decrease bacteria on the skin when water, soap & towel are not available – Recommended for repeated use.

Warnings

For external use only.

Flammable — Keep away from fire or flame.

When using this product keep out of eyes. In case of contact with eyes, rinse thoroughly with water. Do not use on broken or irritated skin.

Stop use and ask a doctor if irritation or redness develop and last more than 72 hours.

Keep out of reach of children.

If swallowed, get medical help or contact a Poison Control Center right away.

Directions

Apply enough product to wet hands. Rub hands together until dry. Supervise children in use of this product.

Other information

- Do not store above 105 °F (40 °C).
- May discolor certain wood surfaces.

Inactive Ingredients

water, carbomer, triethanolamine, glycerin, propylene glycol, fragrance, aloe barbadensis leaf juice.

PRINCIPAL DISPLAY PANEL - 200 ml Bottle Label

HAND
SANITIZER

CONTAINS
70%
ETHYL
ALCOHOL

TOPICAL
SOLUTION

WITH
ALOE VERA

6.7 Fl. Oz. (200 ml)